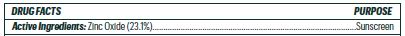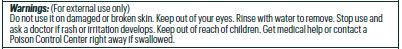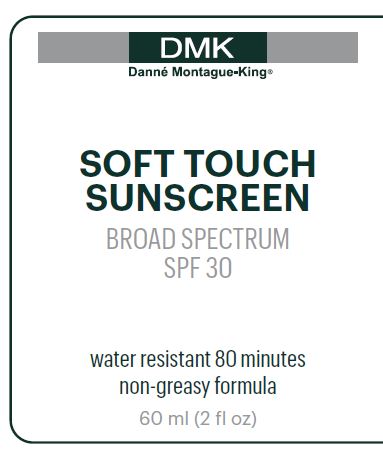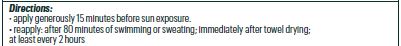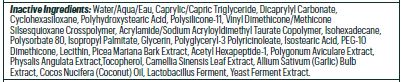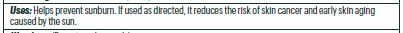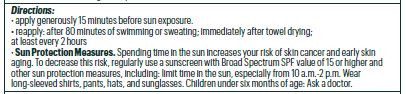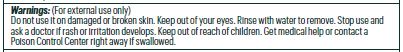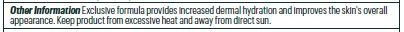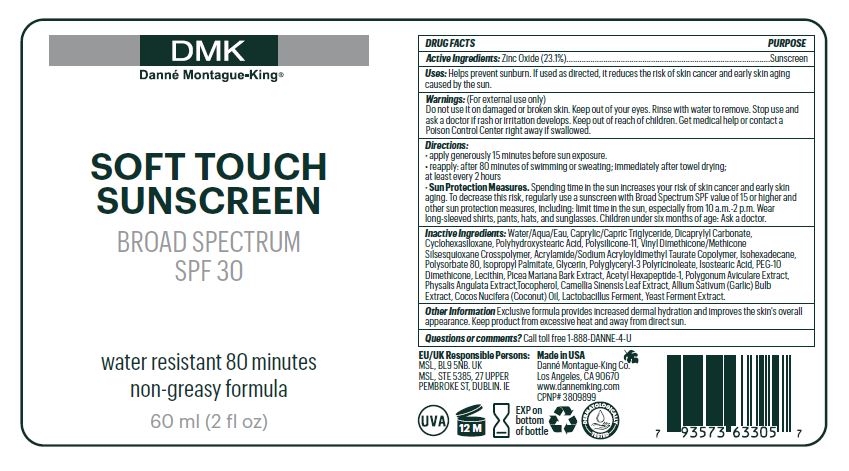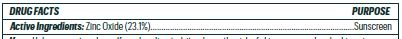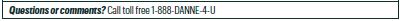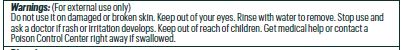 DRUG LABEL: Soft Touch
NDC: 81537-105 | Form: LOTION
Manufacturer: Danne Montague King
Category: otc | Type: HUMAN OTC DRUG LABEL
Date: 20240719

ACTIVE INGREDIENTS: ZINC OXIDE 23.12 g/100 mL
INACTIVE INGREDIENTS: GREEN TEA LEAF 0.7 g/100 mL; CYCLOMETHICONE 6 6.3 g/100 mL; YEAST, UNSPECIFIED 0.2 g/100 mL; DIMETHICONE/VINYL DIMETHICONE CROSSPOLYMER (SOFT PARTICLE) 3.5 g/100 mL; SODIUM ACRYLOYLDIMETHYLTAURATE-ACRYLAMIDE COPOLYMER (1:1; 90000-150000 MPA.S) 1.2 g/100 mL; GARLIC 0.3 g/100 mL; COCONUT OIL 0.3 g/100 mL; POLYGLYCERYL-3 RICINOLEATE 0.68 g/100 mL; POLYSORBATE 80 0.8 g/100 mL; GLYCERIN 0.777 g/100 mL; PEG-10 DIMETHICONE (600 CST) 0.5 g/100 mL; ISOHEXADECANE 1 g/100 mL; WATER 34.858 g/100 mL; MEDIUM-CHAIN TRIGLYCERIDES 9.22 g/100 mL; DICAPRYLYL CARBONATE 8 g/100 mL; VINYL DIMETHICONE/METHICONE SILSESQUIOXANE CROSSPOLYMER 2 g/100 mL; ISOPROPYL PALMITATE 0.8 g/100 mL; ACETYL HEXAPEPTIDE-1 0.025 g/100 mL; POLYGONUM AVICULARE WHOLE 0.02 g/100 mL; PHYSALIS ANGULATA 0.28 g/100 mL; TOCOPHEROL 0.2 g/100 mL; LECITHIN, SOYBEAN 0.49 g/100 mL; ISOSTEARIC ACID 0.68 g/100 mL; POLYHYDROXYSTEARIC ACID (2300 MW) 3.5 g/100 mL

Soft Touch SPF 30